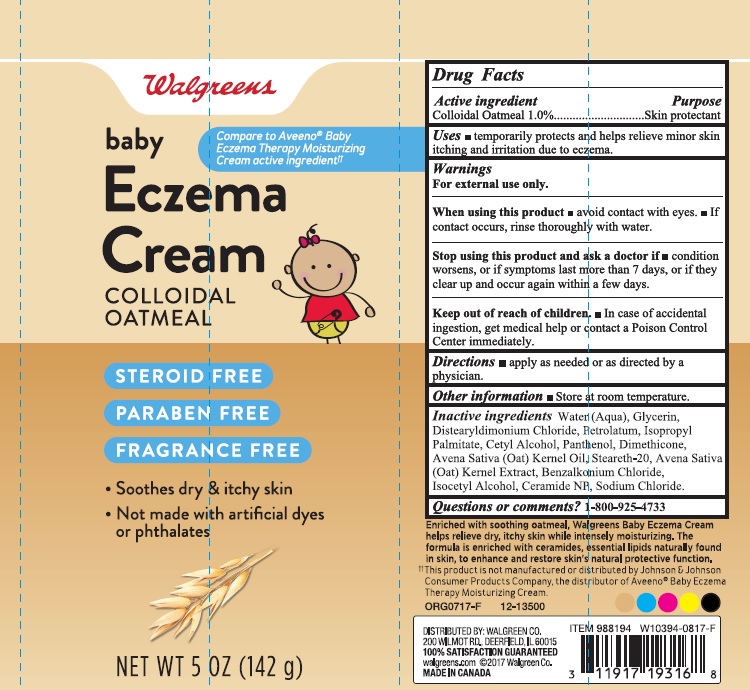 DRUG LABEL: Walgreens Baby Eczema
NDC: 0363-3550 | Form: CREAM
Manufacturer: Walgreen Company
Category: otc | Type: HUMAN OTC DRUG LABEL
Date: 20171129

ACTIVE INGREDIENTS: OATMEAL 0.01 g/1 g
INACTIVE INGREDIENTS: WATER; GLYCERIN; DISTEARYLDIMONIUM CHLORIDE; PETROLATUM; ISOPROPYL PALMITATE; CETYL ALCOHOL; PANTHENOL; DIMETHICONE; OAT; STEARETH-20; OAT KERNEL OIL; BENZALKONIUM CHLORIDE; ISOCETYL ALCOHOL; CERAMIDE NP; SODIUM CHLORIDE

Drug Facts

Active ingredient

Colloidal Oatmeal 1%

Purpose

Skin protectant

Uses

- temporarily protects and helps relieve minor skin itching and irritation due to eczema

Warnings

For external use only

When using this product

- avoid contact with eyes
- if contact occurs, rinse thoroughly with water

Stop using this product and ask a doctor if

- condition worsens, or if symptoms last more than 7 days, or if they clear up and occur again within a few days.

Keep out of reach of children.

- In case of accidental ingestion, get medical help or contact a Poison Control Center immediately.

Directions

- apply as needed or as directed by a physician.

Other information

- store at room temperature

Inactive ingredients

Water (Aqua), Glycerin, Distearyldimonium Chloride, Petrolatum, Isopropyl Palmitate, Cetyl Alcohol, Panthenol, Dimethicone, Avena Sativa (Oat) Kernel Oil, Steareth-20, Avena Sativa (Oat) Kernel Extract, Benzalkonium Chloride, Isocetyl Alcohol, Ceramide NP, Sodium Chloride.

Questions or comments?

1-800-925-4733